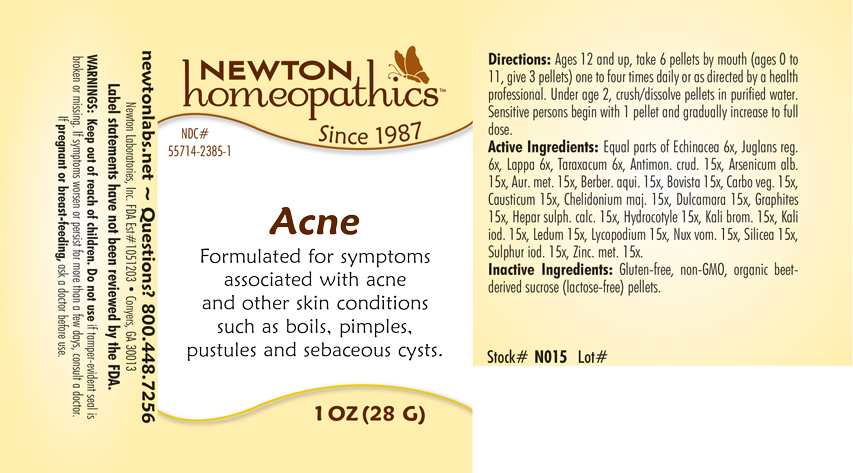 DRUG LABEL: Acne
NDC: 55714-2385 | Form: PELLET
Manufacturer: Newton Laboratories, Inc.
Category: homeopathic | Type: HUMAN OTC DRUG LABEL
Date: 20201124

ACTIVE INGREDIENTS: ANTIMONY TRISULFIDE 15 [hp_X]/1 g; ARSENIC CATION (3+) 15 [hp_X]/1 g; GOLD 15 [hp_X]/1 g; MAHONIA AQUIFOLIUM ROOT BARK 15 [hp_X]/1 g; GIANT PUFFBALL 15 [hp_X]/1 g; ACTIVATED CHARCOAL 15 [hp_X]/1 g; CAUSTICUM 15 [hp_X]/1 g; CHELIDONIUM MAJUS 15 [hp_X]/1 g; SOLANUM DULCAMARA TOP 15 [hp_X]/1 g; GRAPHITE 15 [hp_X]/1 g; CALCIUM SULFIDE 15 [hp_X]/1 g; CENTELLA ASIATICA 15 [hp_X]/1 g; POTASSIUM BROMIDE 15 [hp_X]/1 g; POTASSIUM IODIDE 15 [hp_X]/1 g; LEDUM PALUSTRE TWIG 15 [hp_X]/1 g; LYCOPODIUM CLAVATUM SPORE 15 [hp_X]/1 g; STRYCHNOS NUX-VOMICA SEED 15 [hp_X]/1 g; SILICON DIOXIDE 15 [hp_X]/1 g; SULFUR IODIDE 15 [hp_X]/1 g; ZINC 15 [hp_X]/1 g; ECHINACEA, UNSPECIFIED 6 [hp_X]/1 g; ENGLISH WALNUT 6 [hp_X]/1 g; ARCTIUM LAPPA ROOT 6 [hp_X]/1 g; TARAXACUM OFFICINALE 6 [hp_X]/1 g
INACTIVE INGREDIENTS: SUCROSE

Acne 2385P

OTC - KEEP OUT OF REACH OF CHILDREN SECTION

Keep out of reach of children.

OTC - PREGNANCY OR BREAST FEEDING SECTION

If pregnant or breast-feeding, ask a doctor before use.

WARNINGS SECTION

WARNINGS: Keep out of reach of children. Do not use if tamper-evident seal is broken or missing. If symptoms worsen or persist for more than a few days, consult a doctor. If pregnant or breast-feeding, ask a doctor before use.

QUESTIONS

newtonlabs.net - Questions ? 800 448-7256

Newton Laboratories, Inc. FDA Est # 1051203 - Conyers, GA 300123

INACTIVE INGREDIENT SECTION

Gluten-free, non-GMO, organic beet-derived sucrose (lactose-free) pellets.

DOSAGE & ADMINISTRATION SECTION

Directions: Ages 12 and up, take 6 pellets by mouth (ages 0 to 11, give 3 pellets) one to four times daily or as directed by a health professional. Under age 2, crush/dissolve pellets in purified water. Sensitive persons begin with 1 pellet and gradually increase to full dose.

OTC - PURPOSE SECTION

Formulated for symptoms associated with acne and other skin conditions such as boils, pimples, pustules and sebaceous cysts.

OTC - ACTIVE INGREDIENT SECTION

Equal parts of Echinacea 6x, Juglans reg. 6x, Lappa 6x, Taraxacum 6x, Antimon. crud. 15x, Arsenicum alb. 15x, Aur. met. 15x, Berber. aqui. 15x, Bovista 15x, Carbo veg. 15x, Causticum 15x, Chelidonium maj. 15x, Dulcamara 15x, Graphites 15x, Hepar sulph. calc. 15x, Hydrocotyle 15x, Kali brom. 15x, Kali iod. 15x, Ledum 15x, Lycopodium 15x, Nux vom. 15x, Silicea 15x,Sulphur iod. 15x, Zinc. met. 15x.

INDICATIONS & USAGE SECTION

Formulated for symptoms associated with acne and other skin conditions such as boils, pimples, pustules and sebaceous cysts.